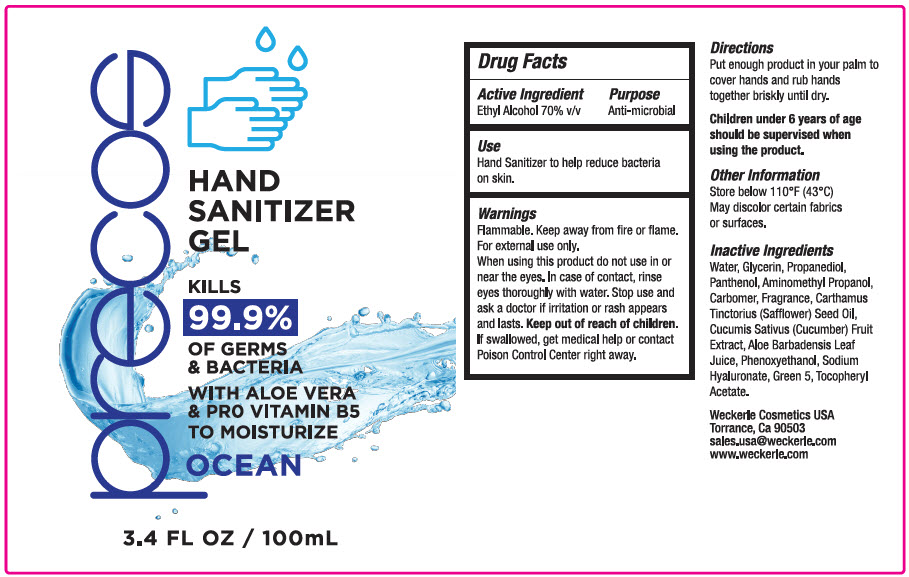 DRUG LABEL: HAND SANITIZER
NDC: 62516-001 | Form: GEL
Manufacturer: Weckerle Cosmetics LLC
Category: otc | Type: HUMAN OTC DRUG LABEL
Date: 20200713

ACTIVE INGREDIENTS: Alcohol 70 mL/100 mL
INACTIVE INGREDIENTS: Water; Glycerin; Propanediol; Panthenol; Aminomethylpropanol; CARBOMER HOMOPOLYMER, UNSPECIFIED TYPE; Safflower Oil; Cucumber; Aloe Vera Leaf; Phenoxyethanol; Hyaluronate Sodium; D&C Green No. 5; .Alpha.-Tocopherol Acetate

HAND SANITIZER

Drug Facts

Active Ingredient

Ethyl Alcohol 70% v/v

Purpose

Anti-microbial

Use

- Hand Sanitizer to help reduce bacteria on skin

Warnings

Flammable. Keep away from fire or flame.

For external use only

When using this product do not use in or near the eyes.

In case of contact, rinse eyes thoroughly with water.

Stop use and ask a doctor if irritation or rash appears and lasts.

Keep out of reach of children. If swallowed, get medical help or contact Poison Control Center right away.

Directions

- Put enough product in your palm to cover hands and rub hands together briskly until dry.
- Children under 6 years of age should be supervised when using the product.

Other Information

- Store below 110°F (43°C)
- May discolor certain fabrics or surfaces

Inactive Ingredients

Water , Glycerin, Propanediol, Panthenol, Aminomethyl Propanol, Carbomer, Fragrance, Carthamus Tinctorius (Safflower) Seed Oil, Cucumis Sativus (Cucumber) Fruit Extract, Aloe Barbadensis Leaf Juice, Phenoxyethanol, Sodium Hyaluronate, Green 5, Tocopheryl Acetate.

PRINCIPAL DISPLAY PANEL - 100 mL Bottle Label

precos

HAND
SANITIZER
GEL

KILLS
99.9%
OF GERMS
& BACTERIA

WITH ALOE VERA
& PRO VITAMIN B5
TO MOISTURIZE

OCEAN

3.4 FL OZ / 100mL